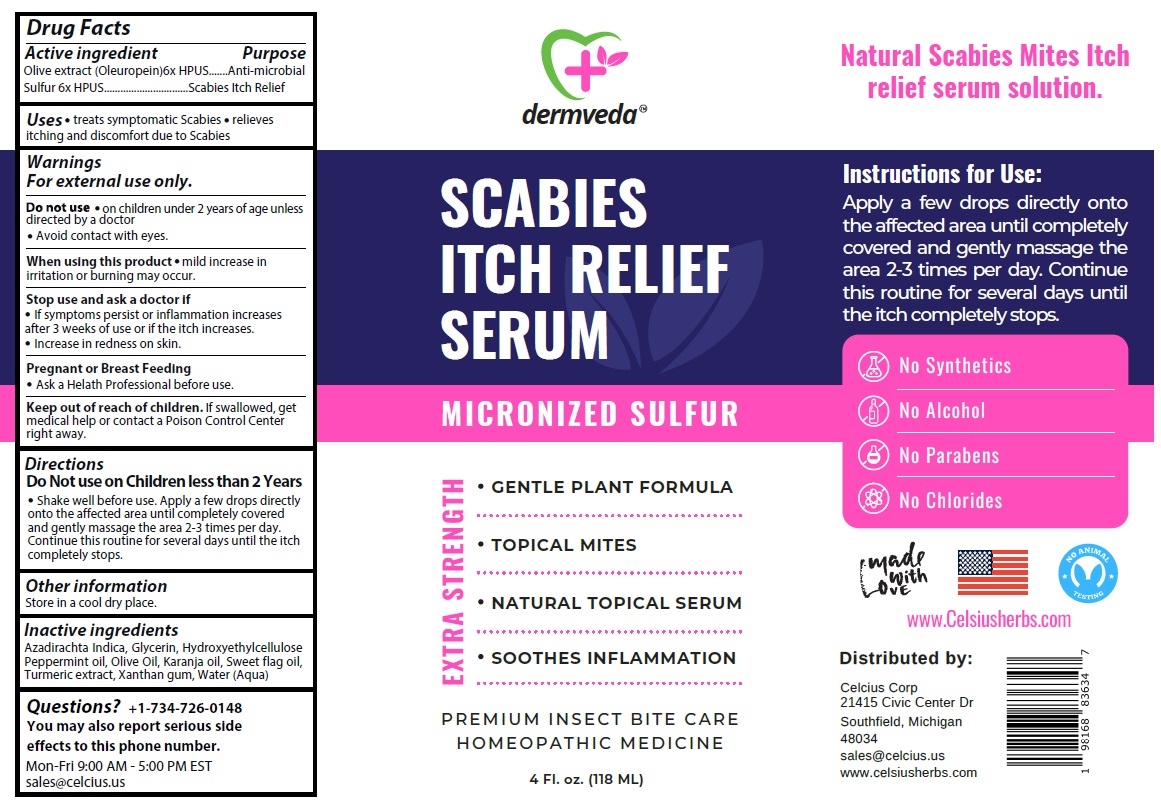 DRUG LABEL: dermveda SCABIES ITCH RELIEF SERUM
NDC: 83819-012 | Form: SOLUTION
Manufacturer: Celcius Corp.
Category: homeopathic | Type: HUMAN OTC DRUG LABEL
Date: 20260209

ACTIVE INGREDIENTS: OLEA EUROPAEA (OLIVE) LEAF POWDER 6 [hp_X]/118 mL; SULFUR 6 [hp_X]/118 mL
INACTIVE INGREDIENTS: AZADIRACHTA INDICA SEED OIL; GLYCERIN; HYDROXYETHYL CELLULOSE, UNSPECIFIED; PEPPERMINT OIL; OLIVE OIL; KARUM SEED OIL; CALAMUS OIL; TURMERIC; XANTHAN GUM; WATER

dermveda™ SCABIES ITCH RELIEF SERUM

Active ingredient

Olive extract (Oleuropein) 6x HPUS
Sulfur 6x HPUS

Purpose

Anti-microbial
Scabies Itch Relief

Uses

• treats symptomatic Scabies • relieves itching and discomfort due to Scabies

Warnings

For external use only.

Do not use • on children under 2 years of age unless directed by a doctor.
• Avoid contact with eyes.

When using this product • mild increase in irritation or burning may occur.

Stop use and ask a doctor if
• If symptoms persist or inflammation increases after 3 weeks of use or if the itch increases.
• Increase in redness on skin.

Pregnant or Breast Feeding
• Ask a Health Professional before use.

Keep out of reach of children. If swallowed, get medical help or contact a Poison Control Center right away.

Directions

Do Not use on Children less than 2 Years

• Shake well before use. Apply a few drops directly onto the affected area until completely covered and gently massage the area 2-3 times per day. Continue this routine for several days until the itch completely stops.

Other information

Store in a cool dry place.

Inactive ingredients

Azadirachta Indica, Glycerin, Hydroxyethylcellulose, Peppermint oil, Olive Oil, Karanja oil, Sweet flag oil, Turmeric extract, Xanthan gum, Water (Aqua)

Questions?

+1-734-726-0148
You may also report serious side effects to this phone number.
Mon-Fri 9:00 AM - 5:00 PM EST

MICRONIZED SULFUR

EXTRA STRENGTH

• GENTLE PLANT FORMULA

• TOPICAL MITES

• NATURAL TOPICAL SERUM

• SOOTHES INFLAMMATION

PREMIUM INSECT BITE CARE
HOMEOPATHIC MEDICINE

Natural Scabies Mites Itch relief serum solution.

No Synthetics
No Alcohol
No Parabens
No Chlorides

made with Love

NO ANIMAL TESTING

Distributed by:

Celcius Corp
21415 Civic Center Dr
Southfield, Michigan
48034
sales@celcius.us
www.celsiusherbs.us